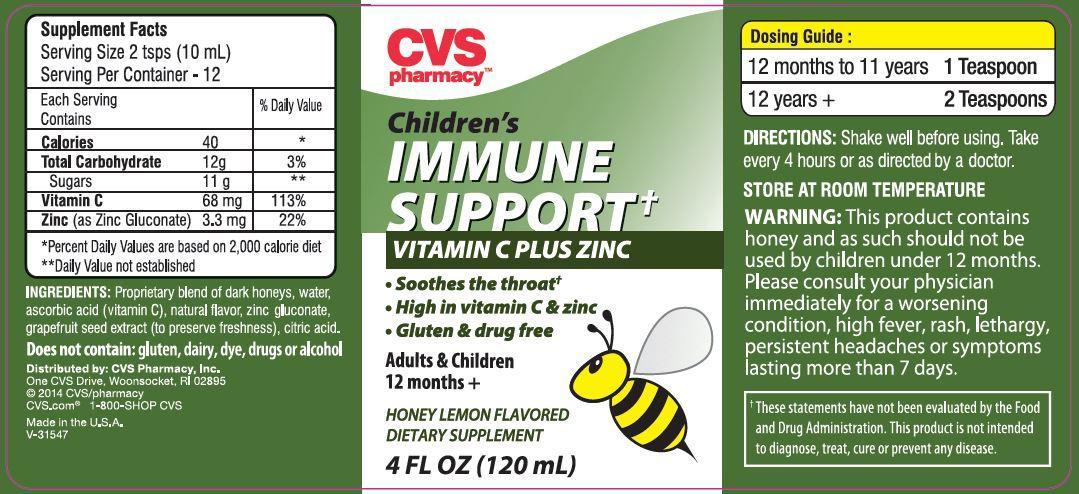 DRUG LABEL: Immune Support
NDC: 59779-859 | Form: LIQUID
Manufacturer: WOONSOCKET PRESCR CTR INC
Category: other | Type: DIETARY SUPPLEMENT
Date: 20141110

ACTIVE INGREDIENTS: ASCORBIC ACID 68 mg/120 mL; ZINC 3 g/120 mL
INACTIVE INGREDIENTS: HONEY; WATER; GRAPEFRUIT SEED OIL; CITRIC ACID MONOHYDRATE

STATEMENT OF IDENTITY

CVS Children's Immune Support†

Vitamin C Plus Zinc

- Soothes the throat†
- High in vitamin C & zinc
- Gluten & drug free

Adults & Children 12 months +

Honey Lemon Flavored Dietary Supplement

4 FL OZ (120 mL)

†These statements have not been evaluated by the Food & Drug Administration. This product is not intended to diagnose, treat, cure or prevent any disease.